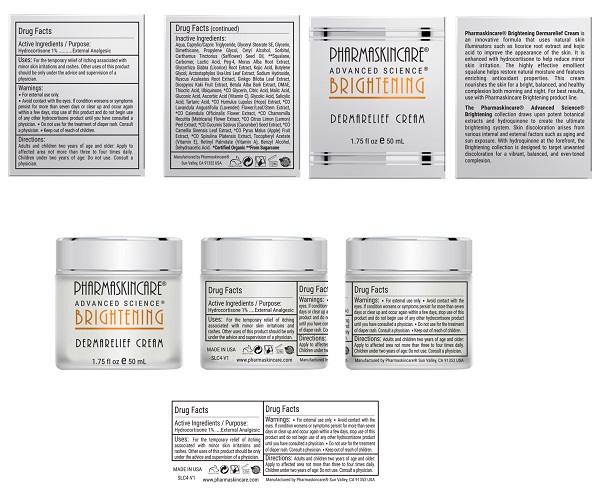 DRUG LABEL: Pharmaskincare Brightening Dermarelief Cream
NDC: 68062-9103 | Form: LOTION
Manufacturer: Spa de Soleil
Category: otc | Type: HUMAN OTC DRUG LABEL
Date: 20171011

ACTIVE INGREDIENTS: HYDROCORTISONE 0.025 mg/2.5 mL
INACTIVE INGREDIENTS: MEDIUM-CHAIN TRIGLYCERIDES; DIMETHICONE; WATER; SAFFLOWER OIL; CETYL ALCOHOL; GLYCERIN; PROPYLENE GLYCOL

Pharmaskincare Brightening Dermarelief Cream

Active Ingredient

Hydrocortisone 1%

Purpose

External Analgesic

Warnings

- For external use only.
- Avoid contact with the eyes
- If condition worsens or symptoms persist for more than seven days or clear up and occur again within a few days, stope use of this product and do not begin use of any hydrocortisone product until you have consulted a physician.
- Do not use for the treatment of diaper rash. Consult a physician.
- Keep out of reach of children.

Directions

Adults and children two years of age and older: Apply to affected area not more than three or four times daily. Children under two years of age: Do not use; consult a physician.

Uses:

For the temporary relief of itching associated with minor skin irritations and rashes. Other uses of this product should be only under the advice and supervision of a physician.

Inactive Ingredients:

Water, Caprylic/Capric Triglyceride, Glyceryl Stearate SE, Glycerin, Dimethicone, Propylene Glycol, Cetyl Alcohol, Sorbitol, Carthamus Tinctorius (Safflower) Seed Oil, **Squalane, Carbomer, Lactic Acid, Peg-4, Morus Alba Root Extract, Glycyrrhiza Glabra (Licorice) Root Extract, Kojic Acid, Butylene Glycol, Arctostaphylos Uva-Ursi Leaf Extract, Sodium Hydroxide, Ruscus Aculeatus Root Extract, Ginkgo Biloba Leaf Extract, Diospyros Kaki Fruit Extract, Betula Alba Bark Extract, DMAE, Thioctic Acid, Ubiquinone, *CO Glycerin, Citric Acid, Malic Acid, Gluconic Acid, Ascorbic Acid (Vitamin C), Malus Domestica Fruit Cell Culture Extract, Glycolic Acid, Salicylic Acid, Tartaric Acid, *CO Humulus Lupulus (Hops) Extract, *CO Lavandula Angustifolia (Lavender) Flower/Leaf/Stem Extract, *CO Calendula Officinalis Flower Extract, *CO Chamomilla Recutita (Matricaria) Flower Extract, *CO Citrus Limon (Lemon) Peel Extract, *CO Cucumis Sativus (Cucumber) Seed Extract, *CO Camellia Sinensis Leaf Extract, *CO Pyrus Malus (Apple) Fruit Extract, *CO Spirulina Platensis Extract, Xanthan Gum, Lecithin, Tocopheryl Acetate (Vitamin E), Retinyl Palmitate (Vitamin A), Benzyl Alcohol, Dehydroacetic Acid

Warning

Keep out of reach of children.

PACKAGE LABEL

Pharmaskincare Brightening Dermarelief.jpg